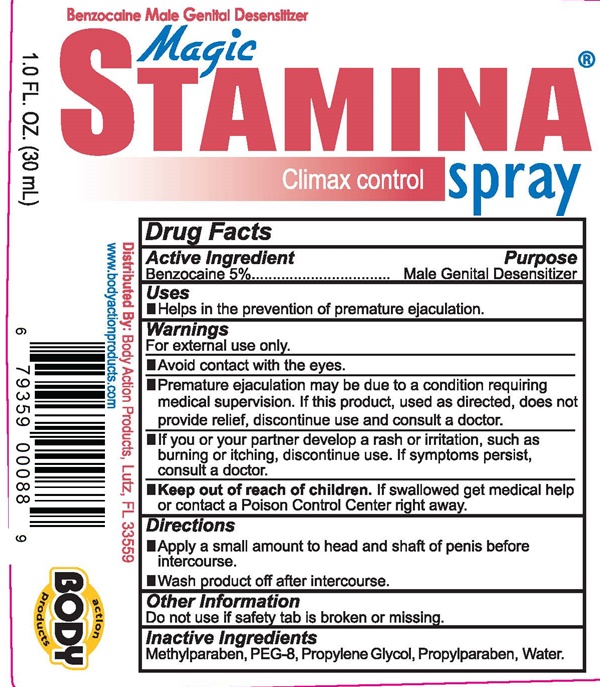 DRUG LABEL: Magic STAMINA
NDC: 70742-088 | Form: LIQUID
Manufacturer: Product Max Group Inc
Category: otc | Type: HUMAN OTC DRUG LABEL
Date: 20160624

ACTIVE INGREDIENTS: BENZOCAINE 1417 mg/30 mL
INACTIVE INGREDIENTS: METHYLPARABEN; POLYETHYLENE GLYCOL 400; PROPYLENE GLYCOL; PROPYLPARABEN; WATER

Magic STAMINA - 088

Drug Facts Active Ingredient

Benzocaine 5%

Purpose

Male Genital Desensitizer

Uses

Helps in the prevention of premature ejaculation.

Warnings

For external use only.

- Avoid contact with eyes
- Premature ejaculation may be due to a condition requiring medical supervision. If this product, used as directed, does not provide relief, discontinue use and consult a doctor.
- If you or your partner develop a rash or irritation, such as burning or itching, discontinue use. if symptoms persist, consult a doctor.

Keep out of reach of children

If swallowed get medical help or contact a Poison Control Center right away.

Directions

- Apply a small amount to head and shaft of penis before intercourse.
- Wash product off after intercourse.

Other Information

Do not use if safety tab is broken or missing.

Inactive Ingredients

Methylparaben, PEG-8, Propylene Glycol, Propylparaben, Water

Magic STAMINA product label

Benzocaine Male genital Desensitizer

Magic STAMINA®

Climax contral spray

1.0 FL. OZ. (30 mL)

Distributed By: Body Action Products, Lutz FL 33559

www.bodyactionproducts.com